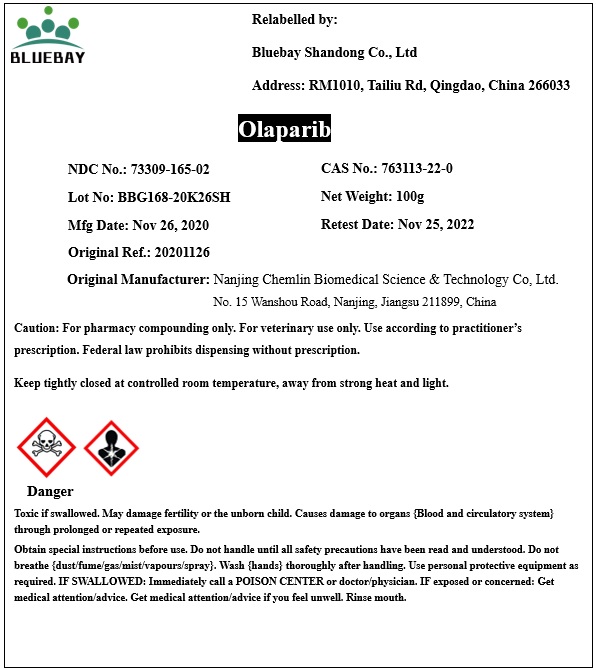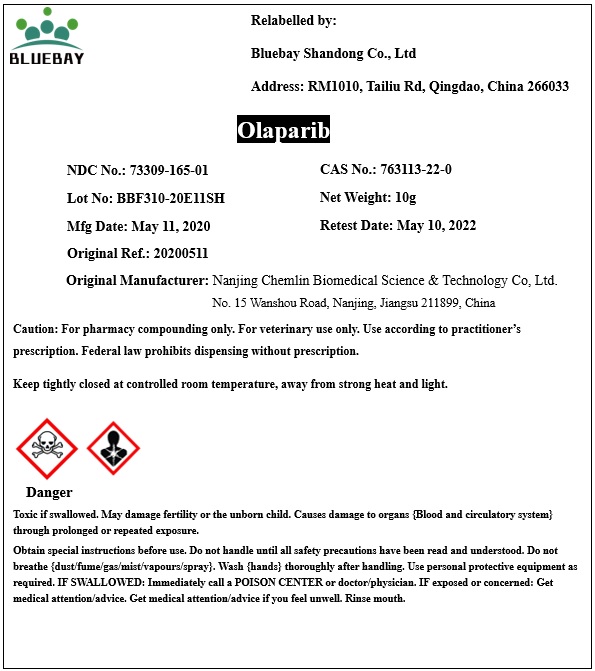 DRUG LABEL: Olaparib
NDC: 73309-165 | Form: POWDER
Manufacturer: BLUEBAY SHANDONG CO.,LTD
Category: other | Type: BULK INGREDIENT
Date: 20210324

ACTIVE INGREDIENTS: OLAPARIB 1 g/1 g

Olaparib